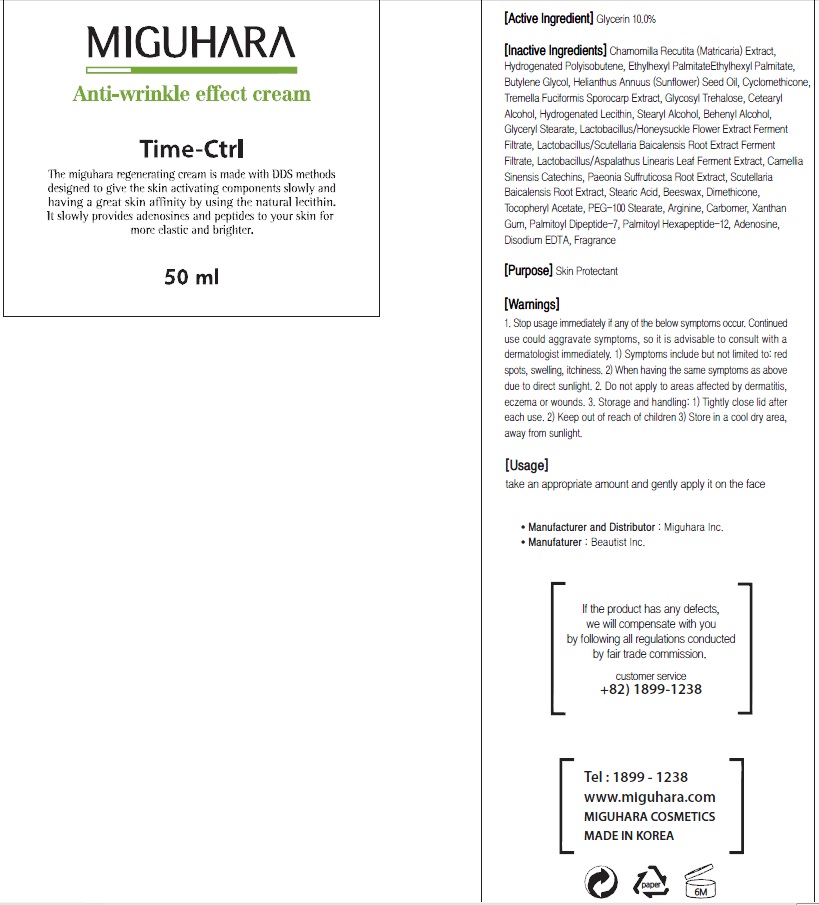 DRUG LABEL: Anti Wrinkle effect
NDC: 70380-100 | Form: CREAM
Manufacturer: MIGUHARA
Category: otc | Type: HUMAN OTC DRUG LABEL
Date: 20160218

ACTIVE INGREDIENTS: Glycerin 5.0 g/50 mL
INACTIVE INGREDIENTS: CHAMOMILE; Butylene Glycol

ACTIVE INGREDIENT

Active Ingredient: Glycerin 10.0%

INACTIVE INGREDIENT

Inactive Ingredients: Chamomilla Recutita (Matricaria) Extract, Hydrogenated Polyisobutene, Ethylhexyl PalmitateEthylhexyl Palmitate, Butylene Glycol, Helianthus Annuus (Sunflower) Seed Oil, Cyclomethicone, Tremella Fuciformis Sporocarp Extract, Glycosyl Trehalose, Cetearyl Alcohol, Hydrogenated Lecithin, Stearyl Alcohol, Behenyl Alcohol, Glyceryl Stearate, Lactobacillus/Honeysuckle Flower Extract Ferment Filtrate, Lactobacillus/Scutellaria Baicalensis Root Extract Ferment Filtrate, Lactobacillus/Aspalathus Linearis Leaf Ferment Extract, Camellia Sinensis Catechins, Paeonia Suffruticosa Root Extract, Scutellaria Baicalensis Root Extract, Stearic Acid, Beeswax, Dimethicone, Tocopheryl Acetate, PEG-100 Stearate, Arginine, Carbomer, Xanthan Gum, Palmitoyl Dipeptide-7, Palmitoyl Hexapeptide-12, Adenosine, Disodium EDTA, Fragrance

PURPOSE

Purpose: Skin Protectant

WARNINGS

1. Stop usage immediately if any of the below symptoms occur. Continued use could aggravate symptoms, so it is advisable to consult with a dermatologist immediately. 1) Symptoms include but not limited to: red spots, swelling, itchiness. 2) When having the same symptoms as above due to direct sunlight. 2. Do not apply to areas affected by dermatitis, eczema or wounds. 3. Storage and handling: 1) Tightly close lid after each use. 2 Keep out of reach of children 3) Store in a cool dry area, away from sunlight

KEEP OUT OF REACH OF CHILDREN

Usage

Usage: Take an appropriate amount and gently apply it on the face.

Usage

Usage: Take an appropriate amount and gently apply it on the face.